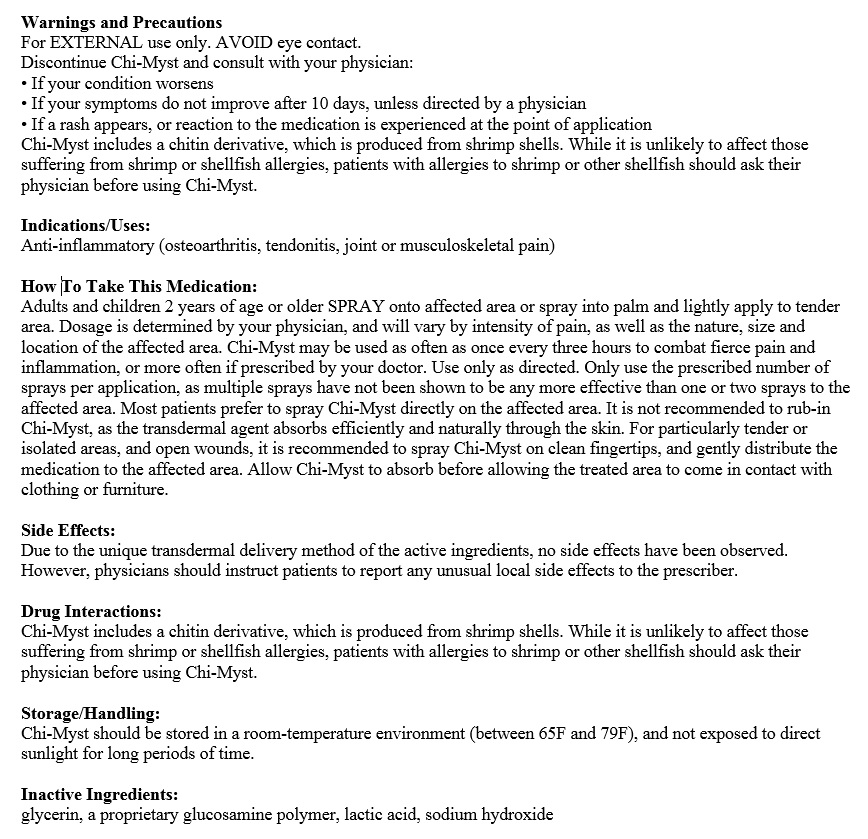 DRUG LABEL: Chi-Myst Synergy
NDC: 70486-030 | Form: SPRAY, METERED
Manufacturer: Prescription Care LLC
Category: prescription | Type: HUMAN PRESCRIPTION DRUG LABEL
Date: 20170113

ACTIVE INGREDIENTS: BUPIVACAINE HYDROCHLORIDE 0.09 g/30 mL; KETOROLAC TROMETHAMINE 0.45 g/30 mL; CHITOSAN LOW MOLECULAR WEIGHT (20-200 MPA.S) 0.03 g/30 mL; LIDOCAINE HYDROCHLORIDE 1.5 g/30 mL
INACTIVE INGREDIENTS: GLYCERIN 0.3 mL/30 mL; WATER 30 mL/30 mL; LACTIC ACID LACTATE, DL- 0.042 mL/30 mL; SODIUM HYDROXIDE 0.01950 g/30 mL

Chi-Myst Synergy Topical